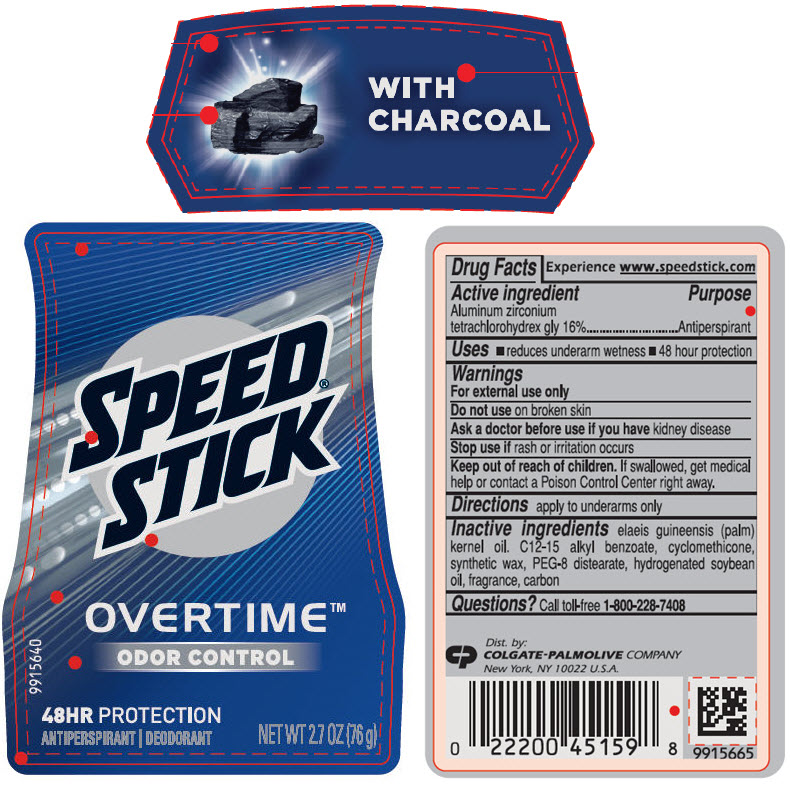 DRUG LABEL: Mens Speed Stick Overtime Odor Control with Charcoal - antiperspirant/deodorant
NDC: 35000-386 | Form: STICK
Manufacturer: COLGATE PALMOLIVE COMPANY
Category: otc | Type: HUMAN OTC DRUG LABEL
Date: 20241106

ACTIVE INGREDIENTS: ALUMINUM ZIRCONIUM TETRACHLOROHYDREX GLY 160 mg/1 g
INACTIVE INGREDIENTS: PALM KERNEL OIL; ALKYL (C12-15) BENZOATE; CYCLOMETHICONE; PEG-8 DISTEARATE; HYDROGENATED SOYBEAN OIL; ACTIVATED CHARCOAL

Mens Speed® Stick Overtime™ Odor Control with Charcoal - antiperspirant/deodorant (2.7 oz)

Drug Facts

Active ingredient

Aluminum zirconium tetrachlorohydrex gly 16%

Purpose

Antiperspirant

Uses

- reduces underarm wetness
- 48 hour protection

Warnings

For external use only

Do not use on broken skin

Ask a doctor before use if you have kidney disease

Stop use if rash or irritation occurs

Keep out of reach of children. If swallowed, get medical help or contact a Poison Control Center right away.

Directions

apply to underarms only

Inactive ingredients

elaeis guineensis (palm) kernel oil. C12-15 alkyl benzoate, cyclomethicone, synthetic wax, PEG-8 distearate, hydrogenated soybean oil, fragrance, carbon

Questions?

Call toll-free 1-800-228-7408

Dist. by:
COLGATE-PALMOLIVE COMPANY
New York, NY 10022 U.S.A.

PRINCIPAL DISPLAY PANEL - 76 g Container

WITH
CHARCOAL

SPEED®
STICK

OVERTIME™
ODOR CONTROL

48HR PROTECTION
ANTIPERSPIRANT | DEODORANT

NET WT 2.7 OZ (76 g)

9915640